DRUG LABEL: Unknown
Manufacturer: Baxter Healthcare Corporation
Category: prescription | Type: HUMAN PRESCRIPTION DRUG LABELING
Date: 20060112

3% and 5% Sodium Chloride Injection, USP

DESCRIPTION

3% and 5% Sodium Chloride Injection, USP is a sterile, nonpyrogenic, hypertonic solution for fluid and electrolyte replenishment in single dose containers for intravenous administration. The pH may have been adjusted with hydrochloric acid. It contains no antimicrobial agents. Composition, ionic concentration, osmolarity, and pH are shown in Table 1.

Table 1
 | Size (mL) | Composition (g/L) | Ionic Concentration (mEq/L) |  | [Normal physiological osmolarity range is approximately 280 to 310 mOsmol/L. Administration of substantially hypertonic solutions (≥ 600 mOsmol/L) may cause vein damage.] Osmolarity (mOsmol/L) (calc) | pH
 | Size (mL) | Sodium Chloride, USP (NaCl) | Sodium | Chloride | [Normal physiological osmolarity range is approximately 280 to 310 mOsmol/L. Administration of substantially hypertonic solutions (≥ 600 mOsmol/L) may cause vein damage.] Osmolarity (mOsmol/L) (calc) | pH
3% Sodium Chloride Injection, USP | 500 | 30 | 513 | 513 | 1027 | 5.0 (4.5 to 7.0)
5% Sodium Chloride Injection, USP | 500 | 50 | 856 | 856 | 1711 | 5.0 (4.5 to 7.0)

The VIAFLEX plastic container is fabricated from a specially formulated polyvinyl chloride (PL 146 Plastic). The amount of water that can permeate from inside the container into the overwrap is insufficient to affect the solution significantly. Solutions in contact with the plastic container can leach out certain of its chemical components in very small amounts within the expiration period, e.g., di-2-ethylhexyl phthalate (DEHP), up to 5 parts per million. However, the safety of the plastic has been confirmed in tests in animals according to USP biological tests for plastic containers as well as by tissue culture toxicity studies.

CLINICAL PHARMACOLOGY

3% and 5% Sodium Chloride Injection, USP has value as a source of water and electrolytes. It is capable of inducing diuresis depending on the clinical condition of the patient.

INDICATIONS AND USAGE

3% and 5% Sodium Chloride Injection, USP is indicated as a source of water and electrolytes.

CONTRAINDICATIONS

None known

WARNINGS

3% and 5% Sodium Chloride Injection, USP is strongly hypertonic and may cause vein damage.

3% and 5% Sodium Chloride Injection, USP should be used with great care, if at all, in patients with congestive heart failure, severe renal insufficiency, and in clinical states in which there exists edema with sodium retention.

In patients with diminished renal function, administration of 3% and 5% Sodium Chloride Injection, USP may result in sodium retention.

GENERAL PRECAUTIONS

Clinical evaluation and periodic laboratory determinations are necessary to monitor changes in fluid balance, electrolyte concentrations, and acid base balance during prolonged parenteral therapy or whenever the condition of the patient warrants such evaluation.

Caution must be exercised in the administration of 3% and 5% Sodium Chloride Injection, USP to patients receiving corticosteroids or corticotropin.

Pregnancy

Teratogenic Effects

Pregnancy Category C

Animal reproduction studies have not been conducted with 3% and 5% Sodium Chloride Injection, USP. It is also not known whether 3% and 5% Sodium Chloride Injection, USP can cause fetal harm when administered to a pregnant woman or can affect reproduction capacity. 3% and 5% Sodium Chloride Injection, USP should be given to a pregnant woman only if clearly needed.

Pediatric Use

Safety and effectiveness of 3% and 5% Sodium Chloride Injection, USP in pediatric patients have not been established by adequate and well controlled trials, however, the use of sodium chloride solutions in the pediatric population is referenced in the medical literature. The warnings, precautions and adverse reactions identified in the label copy should be observed in the pediatric population.

Geriatric Use

Clinical studies of 3% and 5% Sodium Chloride Injection, USP, did not include sufficient numbers of subjects aged 65 and over to determine whether they respond differently from younger subjects. Other reported clinical experience has not identified differences in responses between the elderly and younger patients. In general, dose selection for an elderly patient should be cautious, usually starting at the low end of the dosing range, reflecting the greater frequency of decreased hepatic, renal, or cardiac function, and of concomitant disease or drug therapy.

This drug is known to be substantially excreted by the kidney, and the risk of toxic reactions to this drug may be greater in patients with impaired renal function. Because elderly patients are more likely to have decreased renal function, care should be taken in dose selection, and it may be useful to monitor renal function.

Do not administer unless solution is clear and seal is intact.

ADVERSE REACTIONS

Reactions which may occur because of the solution or the technique of administration include febrile response, infection at the site of injection, venous thrombosis or phlebitis extending from the site of injection, extravasation and hypervolemia.

If an adverse reaction does occur, discontinue the infusion, evaluate the patient, institute appropriate therapeutic countermeasures, and save the remainder of the fluid for examination if deemed necessary.

HOW SUPPLIED

3% and 5% Sodium Chloride Injection, USP in VIAFLEX plastic container is available as follows:

Code | Size (mL) | NDC | Product Name
2b1353 | 500 | 0338-0054-03 | 3% Sodium Chloride Injection, USP
2B1373 | 500 | 0338-0056-03 | 5% Sodium Chloride Injection, USP

Exposure of pharmaceutical products to heat should be minimized. Avoid excessive heat. It is recommended the product be stored at room temperature (25°C); brief exposure up to 40°C does not adversely affect the product.

Directions for Use of VIAFLEX Plastic Container

Warning: Do not use plastic containers in series connections. Such use could result in air embolism due to residual air being drawn from the primary container before administration of the fluid from the secondary container is completed.

To Open

Tear overwrap down side at slit and remove solution container. Some opacity of the plastic due to moisture absorption during the sterilization process may be observed. This is normal and does not affect the solution quality or safety. The opacity will diminish gradually. Check for minute leaks by squeezing inner bag firmly. If leaks are found, discard solution as sterility may be impaired. If supplemental medication is desired, follow directions below.

Preparation for Administration

1. Suspend container from eyelet support.
2. Remove plastic protector from outlet port at bottom of container.
3. Attach administration set. Refer to complete directions accompanying set.

To Add Medication

Warning: Additives may be incompatible.

To add medication before solution administration

1. Prepare medication site
2. Using syringe with 19 to 22 gauge needle, puncture resealable medication port and inject.
3. Mix solution and medication thoroughly. For high density medication such as potassium chloride, squeeze ports while ports are upright and mix thoroughly.

To add medication during solution administration

1. Close clamp on the set.
2. Prepare medication site.
3. Using syringe with 19 to 22 gauge needle, puncture resealable medication port and inject.
4. Remove container from IV pole and/or turn to an upright position.
5. Evacuate both ports by squeezing them while container is in the upright position.
6. Mix solution and medication thoroughly.
7. Return container to in use position and continue administration.

Baxter Healthcare Corporation

Deerfield, IL 60015 USA

Printed in USA